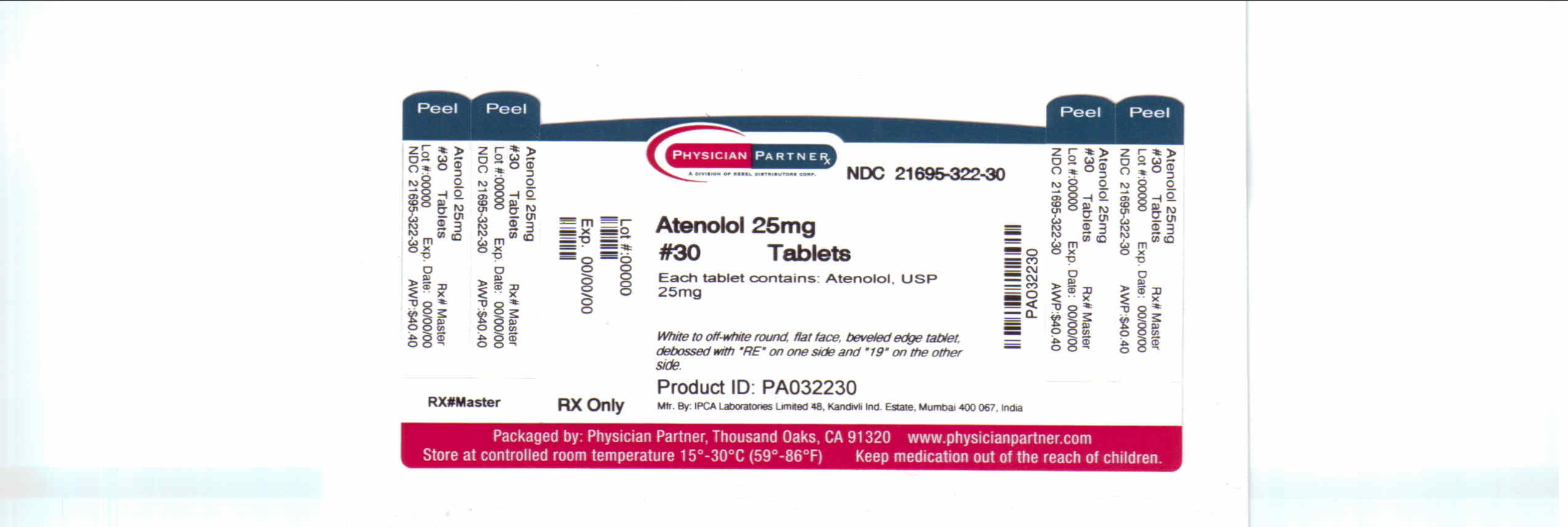 DRUG LABEL: Atenolol
NDC: 21695-322 | Form: TABLET
Manufacturer: Rebel Distributors Corp.
Category: prescription | Type: HUMAN PRESCRIPTION DRUG LABEL
Date: 20110628

ACTIVE INGREDIENTS: ATENOLOL 25 mg/1 1
INACTIVE INGREDIENTS: MAGNESIUM CARBONATE; MAGNESIUM STEARATE; SILICON DIOXIDE; SODIUM LAURYL SULFATE; SODIUM STARCH GLYCOLATE TYPE A POTATO; STARCH, CORN

Atenolol 25 mg

DESCRIPTION

Atenolol, a synthetic, beta1-selective (cardioselective) adrenoreceptor blocking agent, may be chemically described as benzeneacetamide, 4 -[2’-hydroxy-3’-[(1- methylethyl) amino] propoxy]-.

CLINICAL PHARMACOLOGY

Atenolol is a beta1-selective (cardioselective) beta-adrenergic receptor blocking agent without membrane stabilizing or intrinsic sympathomimetic (partial agonist) activities. This preferential effect is not absolute, however, and at higher doses, atenolol inhibits beta2-adrenoreceptors, chiefly located in the bronchial and vascular musculature

Pharmacokinetics and Metabolism

In man, absorption of an oral dose is rapid and consistent but incomplete. Approximately 50% of an oral dose is absorbed from the gastrointestinal tract, the remainder being excreted unchanged in the feces. Peak blood levels are reached between two (2) and four (4) hours after ingestion. Unlike propranolol or metoprolol, but like nadolol, atenolol undergoes little or no metabolism by the liver, and the absorbed portion is eliminated primarily by renal excretion. Over 85% of an intravenous dose is excreted in urine within 24 hours compared with approximately 50% for an oral dose. Atenolol also differs from propranolol in that only a small amount (6% to 16%) is bound to proteins in the plasma. This kinetic profile results in relatively consistent plasma drug levels with about a fourfold interpatient variation.

The elimination half-life of oral atenolol is approximately 6 to 7 hours, and there is no alteration of the kinetic profile of the drug by chronic administration. Following intravenous administration, peak plasma levels are reached within 5 minutes. Declines from peak levels are rapid (5- to 10-fold) during the first 7 hours; thereafter, plasma levels decay with a half-life similar to that of orally administered drug. Following oral doses of 50 mg or 100 mg, both beta-blocking and antihypertensive effects persist for at least 24 hours. When renal function is impaired, elimination of atenolol is closely related to the glomerular filtration rate; significant accumulation occurs when the creatinine clearance falls below 35 mL/min/1.73 m^2. (See DOSAGE AND ADMINISTRATION.)

trend that the elimination of renally excreted drugs is decreased with increasing age

INDICATIONS AND USAGE

Hypertension

Atenolol is indicated in the management of hypertension. It may be used alone or concomitantly with other antihypertensive agents, particularly with a thiazide-type diuretic.

Angina Pectoris Due to Coronary Atherosclerosis

Atenolol is indicated for the long-term management of patients with angina pectoris.

Acute Myocardial Infarction

Atenolol is indicated in the management of hemodynamically stable patients with definite or suspected acute myocardial infarction to reduce cardiovascular mortality. Treatment can be initiated as soon as the patient’s clinical condition allows (see DOSAGE AND ADMINISTRATION, CONTRAINDICATIONS, and WARNINGS). In general, there is no basis for treating patients like those who were excluded from the ISIS-1 trial (blood pressure less than 100 mm Hg systolic, heart rate less than 50 bpm) or have other reasons to avoid beta-blockade. As noted above, some subgroups (e.g., elderly patients with systolic blood pressure below 120 mm Hg) seemed less likely to benefit.

CONTRAINDICATIONS

Atenolol is contraindicated in sinus bradycardia, heart block greater than first degree, cardiogenic shock, and overt cardiac failure (see WARNINGS).

Atenolol is contraindicated in those patients with a history of hypersensitivity to the atenolol or any of the drug product’s components.

WARNINGS

Anaphylactoid and Possibly Related Reactions

Presumably because angiotensin-converting enzyme inhibitors affect the metabolism of eicosanoids and polypeptides, including endogenous bradykinin, patients receiving ACE inhibitors (including ALTACE) may be subject to a variety of adverse reactions, some of them serious.

Head and Neck Angioedema

Patients with a history of angioedema unrelated to ACE inhibitor therapy may be at increased risk of angioedema while receiving an ACE inhibitor. (See also CONTRAINDICATIONS .)

Angioedema of the face, extremities, lips, tongue, glottis, and larynx has been reported in patients treated with angiotensin converting enzyme inhibitors. Angioedema associated with laryngeal edema can be fatal. If laryngeal stridor or angioedema of the face, tongue, or glottis occurs, treatment with ALTACE should be discontinued and appropriate therapy instituted immediately. Where there is involvement of the tongue, glottis, or larynx, likely to cause airway obstruction, appropriate therapy, e.g., subcutaneous epinephrine solution 1:1,000 (0.3 mL to 0.5 mL) should be promptly administered. (See ADVERSE REACTIONS .)

Intestinal Angioedema

Intestinal angioedema has been reported in patients treated with ACE inhibitors. These patients presented with abdominal pain (with or without nausea or vomiting); in some cases there was no prior history of facial angioedema and C-1 esterase levels were normal. The angioedema was diagnosed by procedures including abdominal CT scan or ultrasound, or at surgery, and symptoms resolved after stopping the ACE inhibitor. Intestinal angioedema should be included in the differential diagnosis of patients on ACE inhibitors presenting with abdominal pain.

In a large U.S. postmarketing study, angioedema (defined as reports of angio, face, larynx, tongue, or throat edema) was reported in 3/1523 (0.20%) of black patients and in 8/8680 (0.09%) of white patients. These rates were not different statistically.

Anaphylactoid reactions during desensitization:

Two patients undergoing desensitizing treatment with hymenoptera venom while receiving ACE inhibitors sustained life-threatening anaphylactoid reactions. In the same patients, these reactions were avoided when ACE inhibitors were temporarily withheld, but they reappeared upon inadvertent rechallenge.

Anaphylactoid reactions during membrane exposure:

Anaphylactoid reactions have been reported in patients dialyzed with high-flux membranes and treated concomitantly with an ACE inhibitor. Anaphylactoid reactions have also been reported in patients undergoing low-density lipoprotein apheresis with dextran sulfate absorption.

Hypotension

ALTACE can cause symptomatic hypotension, after either the initial dose or a later dose when the dosage has been increased. Ramipril has been only rarely associated with hypotension in uncomplicated hypertensive patients. Symptomatic hypotension is most likely to occur in patients who have been volume- and/or salt-depleted as a result of prolonged diuretic therapy, dietary salt restriction, dialysis, diarrhea, or vomiting. Volume and/or salt depletion should be corrected before initiating therapy with ALTACE.

In patients with congestive heart failure, with or without associated renal insufficiency, ACE inhibitor therapy may cause excessive hypotension, which may be associated with oliguria or azotemia and, rarely, with acute renal failure and death. In such patients, ALTACE therapy should be started under close medical supervision; they should be followed closely for the first 2 weeks of treatment and whenever the dose of ramipril or diuretic is increased.

If hypotension occurs, the patient should be placed in a supine position and, if necessary, treated with intravenous infusion of physiological saline. ALTACE treatment usually can be continued following restoration of blood pressure and volume.

Hepatic Failure

Rarely, ACE inhibitors, including ALTACE, have been associated with a syndrome that starts with cholestatic jaundice and progresses to fulminant hepatic necrosis and (sometimes) death. The mechanism of this syndrome is not understood. Patients receiving ACE inhibitors who develop jaundice or marked elevations of hepatic enzymes should discontinue the ACE inhibitor and receive appropriate medical follow-up.

Neutropenia/Agranulocytosis

As with other ACE inhibitors, rarely, a mild- in isolated cases severe- reduction in the red blood cell count and hemoglobin content, white blood cell or platelet count may develop. In isolated cases, agranulocytosis, pancytopenia, and bone marrow depression may occur. Hematological reactions to ACE inhibitors are more likely to occur in patients with collagen vascular disease (e.g. systemic lupus erythematosus, scleroderma) and renal impairment. Monitoring of white blood cell counts should be considered in patients with collagen vascular disease, especially if the disease is associated with impaired renal function.

Fetal/Neonatal Morbidity and Mortality

ACE inhibitors can cause fetal and neonatal morbidity and death when administered to pregnant women. Several dozen cases have been reported in the world literature. When pregnancy is detected, ACE inhibitors should be discontinued as soon as possible.

The use of ACE inhibitors during the second and third trimesters of pregnancy has been associated with fetal and neonatal injury, including hypotension, neonatal skull hypoplasia, anuria, reversible or irreversible renal failure, and death. Oligohydramnios has also been reported, presumably resulting from decreased fetal renal function; oligohydramnios in this setting has been associated with fetal limb contractures, craniofacial deformation, and hypoplastic lung development. Prematurity, intrauterine growth retardation, and patent ductus arteriosus have also been reported, although it is not clear whether these occurrences were due to the ACE inhibitor exposure.

In a published retrospective epidemiological study, infants whose mothers had taken an ACE inhibitor during their first trimester of pregnancy appeared to have an increased risk of major congenital malformations compared with infants whose mothers had not undergone first trimester exposure to ACE inhibitor drugs. The number of cases of birth defects is small and the findings of this study have not yet been confirmed.

Rarely (probably less often than once in every thousand pregnancies), no alternative to ACE inhibitors will be found. In these rare cases, the mothers should be apprised of the potential hazards to their fetuses, and serial ultrasound examinations should be performed to assess the intraamniotic environment.

If oligohydramnios is observed, ALTACE should be discontinued unless it is considered life-saving for the mother. Contraction stress testing (CST), a non-stress test (NST), or biophysical profiling (BPP) may be appropriate, depending upon the week of pregnancy. Patients and physicians should be aware, however, that oligohydramnios may not appear until after the fetus has sustained irreversible injury.

Infants with histories of in utero exposure to ACE inhibitors should be closely observed for hypotension, oliguria, and hyperkalemia. If oliguria occurs, attention should be directed toward support of blood pressure and renal perfusion. Exchange transfusion or dialysis may be required as means of reversing hypotension and/or substituting for disordered renal function. ALTACE which crosses the placenta can be removed from the neonatal circulation by these means, but limited experience has not shown that such removal is central to the treatment of these infants.

No teratogenic effects of ALTACE (ramipril) were seen in studies of pregnant rats, rabbits, and cynomolgus monkeys. On a body surface area basis, the doses used were up to approximately 400 times (in rats and monkeys) and 2 times (in rabbits) the recommended human dose.

PRECAUTIONS

Impaired Renal Function: As a consequence of inhibiting the renin-angiotensin-aldosterone system, changes in renal function may be anticipated in susceptible individuals. In patients with severe congestive heart failure whose renal function may depend on the activity of the renin-angiotensin-aldosterone system, treatment with angiotensin converting enzyme inhibitors, including ALTACE, may be associated with oliguria and/or progressive azotemia and (rarely) with acute renal failure and/or death.

In hypertensive patients with unilateral or bilateral renal artery stenosis, increases in blood urea nitrogen and serum creatinine may occur. Experience with another angiotensin converting enzyme inhibitor suggests that these increases are usually reversible upon discontinuation of ALTACE and/or diuretic therapy. In such patients renal function should be monitored during the first few weeks of therapy. Some hypertensive patients with no apparent pre-existing renal vascular disease have developed increases in blood urea nitrogen and serum creatinine, usually minor and transient, especially when ALTACE has been given concomitantly with a diuretic. This is more likely to occur in patients with pre-existing renal impairment. Dosage reduction of ALTACE and/or discontinuation of the diuretic may be required.

Evaluation of the hypertensive patient should always include assessment of renal function. (See DOSAGE AND ADMINISTRATION .)

Hyperkalemia: In clinical trials, hyperkalemia (serum potassium greater than 5.7 mEq/L) occurred in approximately 1% of hypertensive patients receiving ALTACE. In most cases, these were isolated values, which resolved despite continued therapy. None of these patients was discontinued from the trials because of hyperkalemia. Risk factors for the development of hyperkalemia include renal insufficiency, diabetes mellitus, and the concomitant use of potassium-sparing diuretics, potassium supplements, and/or potassium-containing salt substitutes, which should be used cautiously, if at all, with ALTACE. (See Drug Interactions .)

Cough: Presumably due to the inhibition of the degradation of endogenous bradykinin, persistent nonproductive cough has been reported with all ACE inhibitors, always resolving after discontinuation of therapy. ACE inhibitor-induced cough should be considered in the differential diagnosis of cough.

Impaired Liver Function: Since ramipril is primarily metabolized by hepatic esterases to its active moiety, ramiprilat, patients with impaired liver function could develop markedly elevated plasma levels of ramipril. No formal pharmacokinetic studies have been carried out in hypertensive patients with impaired liver function. However, since the renin-angiotensin system may be activated in patients with severe liver cirrhosis and/or ascites, particular caution should be exercised in treating these patients.

Surgery/Anesthesia: In patients undergoing surgery or during anesthesia with agents that produce hypotension, ramipril may block angiotensin II formation that would otherwise occur secondary to compensatory renin release. Hypotension that occurs as a result of this mechanism can be corrected by volume expansion.

Information for Patients

Pregnancy: Female patients of childbearing age should be told about the consequences of exposure to ACE inhibitors during pregnancy. These patients should be asked to report pregnancies to their physicians as soon as possible.

Angioedema: Angioedema, including laryngeal edema, can occur with treatment with ACE inhibitors, especially following the first dose. Patients should be so advised and told to report immediately any signs or symptoms suggesting angioedema (swelling of face, eyes, lips, or tongue, or difficulty in breathing) and to take no more drug until they have consulted with the prescribing physician.

Symptomatic Hypotension: Patients should be cautioned that lightheadedness can occur, especially during the first days of therapy, and it should be reported. Patients should be told that if syncope occurs, ALTACE should be discontinued until the physician has been consulted.

All patients should be cautioned that inadequate fluid intake or excessive perspiration, diarrhea, or vomiting can lead to an excessive fall in blood pressure, with the same consequences of lightheadedness and possible syncope.

Hyperkalemia: Patients should be told not to use salt substitutes containing potassium without consulting their physician.

Neutropenia: Patients should be told to promptly report any indication of infection (e.g., sore throat, fever), which could be a sign of neutropenia.

Drug Interactions

Gold: Nitritoid reactions (symptoms include facial flushing, nausea, vomiting and hypotension) have been reported rarely in patients on therapy with injectable gold (sodium aurothiomalate) and concomitant ACE inhibitor therapy including ALTACE.

With nonsteroidal anti-inflammatory agents: Rarely, concomitant treatment with ACE inhibitors and nonsteroidal anti-inflammatory agents have been associated with worsening of renal failure and an increase in serum potassium.

With diuretics: Patients on diuretics, especially those in whom diuretic therapy was recently instituted, may occasionally experience an excessive reduction of blood pressure after initiation of therapy with ALTACE. The possibility of hypotensive effects with ALTACE can be minimized by either discontinuing the diuretic or increasing the salt intake prior to initiation of treatment with ALTACE. If this is not possible, the starting dose should be reduced. (See DOSAGE AND ADMINISTRATION .)

With potassium supplements and potassium-sparing diuretics: ALTACE can attenuate potassium loss caused by thiazide diuretics. Potassium-sparing diuretics (spironolactone, amiloride, triamterene, and others) or potassium supplements can increase the risk of hyperkalemia. Therefore, if concomitant use of such agents is indicated, they should be given with caution, and the patient’s serum potassium should be monitored frequently.

With lithium: Increased serum lithium levels and symptoms of lithium toxicity have been reported in patients receiving ACE inhibitors during therapy with lithium. These drugs should be coadministered with caution, and frequent monitoring of serum lithium levels is recommended. If a diuretic is also used, the risk of lithium toxicity may be increased.

Other: Neither ALTACE nor its metabolites have been found to interact with food, digoxin, antacid, furosemide, cimetidine, indomethacin, and simvastatin. The combination of ALTACE and propranolol showed no adverse effects on dynamic parameters (blood pressure and heart rate). The co-administration of ALTACE and warfarin did not adversely affect the anticoagulant effects of the latter drug. Additionally, co-administration of ALTACE with phenprocoumon did not affect minimum phenprocoumon levels or interfere with the subjects’ state of anti-coagulation.

Carcinogenesis, Mutagenesis, Impairment of Fertility

No evidence of a tumorigenic effect was found when ramipril was given by gavage to rats for up to 24 months at doses of up to 500 mg/kg/day or to mice for up to 18 months at doses of up to 1000 mg/kg/day. (For either species, these doses are about 200 times the maximum recommended human dose when compared on the basis of body surface area.) No mutagenic activity was detected in the Ames test in bacteria, the micronucleus test in mice, unscheduled DNA synthesis in a human cell line, or a forward gene-mutation assay in a Chinese hamster ovary cell line. Several metabolites and degradation products of ramipril were also negative in the Ames test. A study in rats with dosages as great as 500 mg/kg/day did not produce adverse effects on fertility.

Pregnancy

Pregnancy Categories C (first trimester) and D (second and third trimesters). See WARNINGS: Fetal/Neonatal Morbidity and Mortality .

Nursing Mothers

Ingestion single 10 mg oral dose of ALTACE resulted in undetectable amounts of ramipril and its metabolites in breast milk. However, because multiple doses may produce low milk concentrations that are not predictable from single doses, women receiving ALTACE should not breast feed.

Geriatric Use

Of the total number of patients who received ramipril in US clinical studies of ALTACE 11.0% were 65 and over while 0.2% were 75 and over. No overall differences in effectiveness or safety were observed between these patients and younger patients, and other, reported clinical experience has not identified differences in responses between the elderly and younger patients, but greater sensitivity of some older individuals cannot be ruled out.

One pharmacokinetic study conducted in hospitalized elderly patients indicated that peak ramiprilat levels and area under the plasma concentration time curve (AUC) for ramiprilat are higher in older patients.

Pediatric Use

Safety and effectiveness in pediatric patients have not been established. Irreversible kidney damage has been observed in very young rats given a single dose of ramipril.

ADVERSE REACTIONS

Hypertension

ALTACE has been evaluated for safety in over 4,000 patients with hypertension; of these, 1,230 patients were studied in US controlled trials, and 1,107 were studied in foreign controlled trials. Almost 700 of these patients were treated for at least one year. The overall incidence of reported adverse events was similar in ALTACE and placebo patients. The most frequent clinical side effects (possibly or probably related to study drug) reported by patients receiving ALTACE in US placebo-controlled trials were: headache (5.4%), “dizziness” (2.2%) and fatigue or asthenia (2.0%), but only the last was more common in ALTACE patients than in patients given placebo. Generally, the side effects were mild and transient, and there was no relation to total dosage within the range of 1.25 to 20 mg. Discontinuation of therapy because of a side effect was required in approximately 3% of US patients treated with ALTACE. The most common reasons for discontinuation were: cough (1.0%), “dizziness” (0.5%), and impotence (0.4%).

Of observed side effects considered possibly or probably related to study drug that occurred in US placebo-controlled trials in more than 1% of patients treated with ALTACE, only asthenia (fatigue) was more common on ALTACE than placebo (2% vs 1%).

PATIENTS IN US PLACEBO CONTROLLED STUDIES
 | ALTACE; (n=651) | Placebo; (n=286)
 | n | % | n | %
Asthenia (Fatigue) | 13 | 2 | 2 | 1

In placebo-controlled trials, there was also an excess of upper respiratory infection and flu syndrome in the ramipril group, not attributed at that time to ramipril. As these studies were carried out before the relationship of cough to ACE inhibitors was recognized, some of these events may represent ramipril-induced cough. In a later 1-year study, increased cough was seen in almost 12% of ramipril patients, with about 4% of these patients requiring discontinuation of treatment.

Heart Failure Post Myocardial Infarction

Adverse reactions (except laboratory abnormalities) considered possibly/probably related to study drug that occurred in more than one percent of patients and more frequently on ramipril are shown below. The incidences represent the experiences from the AIRE study. The follow-up time was between 6 and 46 months for this study.

Percentage of Patients with Adverse Events Possibly/ Probably Related to Study Drug

Placebo-Controlled (AIRE) Mortality Study:

Adverse Event | RAMIPRIL (N=1004) | PLACEBO (N=982)
Hypotension | 11 | 5
Cough Increased | 8 | 4
Dizziness | 4 | 3
Angina Pectoris | 3 | 2
Nausea | 2 | 1
Postural Hypotension | 2 | 1
Syncope | 2 | 1
Vomiting | 2 | 0.5
Vertigo | 2 | 0.7
Abnormal Kidney Function | 1 | 0.5
Diarrhea | 1 | 0.4

HOPE Study:

Safety data in the HOPE trial were collected as reasons for discontinuation or temporary interruption of treatment. The incidence of cough was similar to that seen in the AIRE trial. The rate of angioedema was the same as in previous clinical trials (see WARNINGS).

 | RAMIPRIL; (N=4645) | PLACEBO; (N=4652)
 | % | %
Discontinuation at any time | 34 | 32
Permanent discontinuation | 29 | 28
Reasons for stopping Cough | 7 | 2
Hypotension or Dizziness | 1.9 | 1.5
Angioedema | 0.3 | 0.1

Other adverse experiences reported in controlled clinical trials (in less than 1% of ramipril patients), or rarer events seen in postmarketing experience, include the following (in some, a causal relationship to drug use is uncertain):

Body As a Whole: Anaphylactoid reactions. (See WARNINGS .)

Cardiovascular: Symptomatic hypotension (reported in 0.5% of patients in US trials) (See WARNINGS and PRECAUTIONS), syncope and palpitations.

Hematologic: Pancytopenia, hemolytic anemia and thrombocytopenia.

Renal: Some hypertensive patients with no apparent pre-existing renal disease have developed minor, usually transient, increases in blood urea nitrogen and serum creatinine when taking ALTACE, particularly when ALTACE was given concomitantly with a diuretic. (See WARNINGS .) Acute renal failure.

Angioneurotic Edema: Angioneurotic edema has been reported in 0.3% of patients in US clinical trials. (See WARNINGS .)

Gastrointestinal: Hepatic failure, hepatitis, jaundice, pancreatitis, abdominal pain (sometimes with enzyme changes suggesting pancreatitis), anorexia, constipation, diarrhea, dry mouth, dyspepsia, dysphagia, gastroenteritis, increased salivation and taste disturbance.

Dermatologic: Apparent hypersensitivity reactions (manifested by urticaria, pruritus, or rash, with or without fever), photosensitivity, purpura, onycholysis, pemphigus, pemphigoid, erythema multiforme, toxic epidermal necrolysis, and Stevens-Johnson syndrome.

Neurologic and Psychiatric: Anxiety, amnesia, convulsions, depression, hearing loss, insomnia, nervousness, neuralgia, neuropathy, paresthesia, somnolence, tinnitus, tremor, vertigo, and vision disturbances.

Miscellaneous: As with other ACE inhibitors, a symptom complex has been reported which may include a positive ANA, an elevated erythrocyte sedimentation rate, arthralgia/arthritis, myalgia, fever, vasculitis, eosinophilia, photosensitivity, rash and other dermatologic manifestations. Additionally, as with other ACE inhibitors, eosinophilic pneumonitis has been reported.

Fetal/Neonatal Morbidity and Mortality. See WARNINGS: Fetal/Neonatal Morbidity and Mortality .

Other: Arthralgia, arthritis, dyspnea, edema, epistaxis, impotence, increased sweating, malaise, myalgia, and weight gain.

Post-Marketing Experience: In addition to adverse events reported from clinical trials, there have been rare reports of hypoglycemia reported during ALTACE therapy when given to patients concomitantly taking oral hypoglycemic agents or insulin. The causal relationship is unknown.

Clinical Laboratory Test Findings

Creatinine and Blood Urea Nitrogen: Increases in creatinine levels occurred in 1.2% of patients receiving ALTACE alone, and in 1.5% of patients receiving ALTACE and a diuretic. Increases in blood urea nitrogen levels occurred in 0.5% of patients receiving ALTACE alone and in 3% of patients receiving ALTACE with a diuretic. None of these increases required discontinuation of treatment. Increases in these laboratory values are more likely to occur in patients with renal insufficiency or those pretreated with a diuretic and, based on experience with other ACE inhibitors, would be expected to be especially likely in patients with renal artery stenosis. (See WARNINGS and PRECAUTIONS .) Since ramipril decreases aldosterone secretion, elevation of serum potassium can occur. Potassium supplements and potassium-sparing diuretics should be given with caution, and the patient’s serum potassium should be monitored frequently. (See WARNINGS and PRECAUTIONS .)

Hemoglobin and Hematocrit: Decreases in hemoglobin or hematocrit (a low value and a decrease of 5 g/dL or 5% respectively) were rare, occurring in 0.4% of patients receiving ALTACE alone and in 1.5% of patients receiving ALTACE plus a diuretic. No US patients discontinued treatment because of decreases in hemoglobin or hematocrit.

Other (causal relationships unknown): Clinically important changes in standard laboratory tests were rarely associated with ALTACE administration. Elevations of liver enzymes, serum bilirubin uric acid, and blood glucose have been reported, as have cases of hyponatremia and scattered incidents of leukopenia, eosinophilia, and proteinuria. In US trials, less than 0.2% of patients discontinued treatment for laboratory abnormalities; all of these were cases of proteinuria or abnormal liver-function tests.

OVERDOSAGE

Overdosage with atenolol has been reported with patients surviving acute doses as high as 5 g. One death was reported in a man who may have taken as much as 10 g acutely.

The predominant symptoms reported following atenolol overdose are lethargy, disorder of respiratory drive, wheezing, sinus pause and bradycardia. Additionally, common effects associated with overdosage of any beta-adrenergic blocking agent and which might also be expected in atenolol overdose are congestive heart failure, hypotension, bronchospasm and/or hypoglycemia.

Treatment of overdose should be directed to the removal of any unabsorbed drug by induced emesis, gastric lavage, or administration of activated charcoal. Atenolol can be removed from the general circulation by hemodialysis. Other treatment modalities should be employed at the physician’s discretion and may include:

BRADYCARDIA: Atropine intravenously. If there is no response to vagal blockade, give isoproterenol cautiously. In refractory cases, a transvenous cardiac pacemaker may be indicated.

HEART BLOCK (SECOND OR THIRD DEGREE): Isoproterenol or transvenous cardiac pacemaker.

CARDIAC FAILURE: Digitalize the patient and administer a diuretic. Glucagon has been reported to be useful.

HYPOTENSION: Vasopressors such as dopamine or norepinephrine (levarterenol). Monitor blood pressure continuously.

BRONCHOSPASM: A beta2 stimulant such as isoproterenol or terbutaline and/or aminophylline.

HYPOGLYCEMIA: Intravenous glucose.

Based on the severity of symptoms, management may require intensive support care and facilities for applying cardiac and respiratory support.

DOSAGE AND ADMINISTRATION

Blood pressure decreases associated with any dose of ALTACE depend, in part, on the presence or absence of volume depletion (e.g., past and current diuretic use) or the presence or absence of renal artery stenosis. If such circumstances are suspected to be present, the initial starting dose should be 1.25 mg once daily.

Reduction in Risk of Myocardial Infarction, Stroke, and Death from Cardiovascular Causes

ALTACE should be given at an initial dose of 2.5 mg, once a day for 1 week, 5 mg, once a day for the next 3 weeks, and then increased as tolerated, to a maintenance dose of 10 mg, once a day. If the patient is hypertensive or recently post myocardial infarction, it can also be given as a divided dose.

Hypertension

The recommended initial dose for patients to be treated for hypertension, not receiving a diuretic is 2.5 mg once a day. Dosage should be adjusted according to the blood pressure response. The usual maintenance dosage range is 2.5 to 20 mg per day administered as a single dose or in two equally divided doses. In some patients treated once daily, the antihypertensive effect may diminish toward the end of the dosing interval. In such patients, an increase in dosage or twice daily administration should be considered. If blood pressure is not controlled with ALTACE alone, a diuretic can be added

HOW SUPPLIED

Atenolol Tablets, USP

Each 25 mg atenolol tablet, USP is available as white to off-white round, flat face, beveled edge tablet, debossed with 'RE' on one side and ‘19’ on the other side. They are supplied as follows:

NDC 21695-322-30 Bottles of 30

NDC 21695-322-90 Bottles of 90

Store at 20 - 25°C (68 - 77°F). (See USP Controlled Room Temperature).

Dispense in well-closed, light-resistant containers.

Call your doctor for medical advice about side effects. You may report side effects to FDA at 1-800-FDA-1088.

Manufactured for:

Ranbaxy Pharmaceuticals Inc.

Jacksonville, FL 32257 USA

by: Ipca Laboratories Limited

48, Kandivli Ind. Estate, Mumbai 400 067, India

April 2009

Repackaged by:

Rebel Distributors Corp.

Thousand Oaks, CA 91320